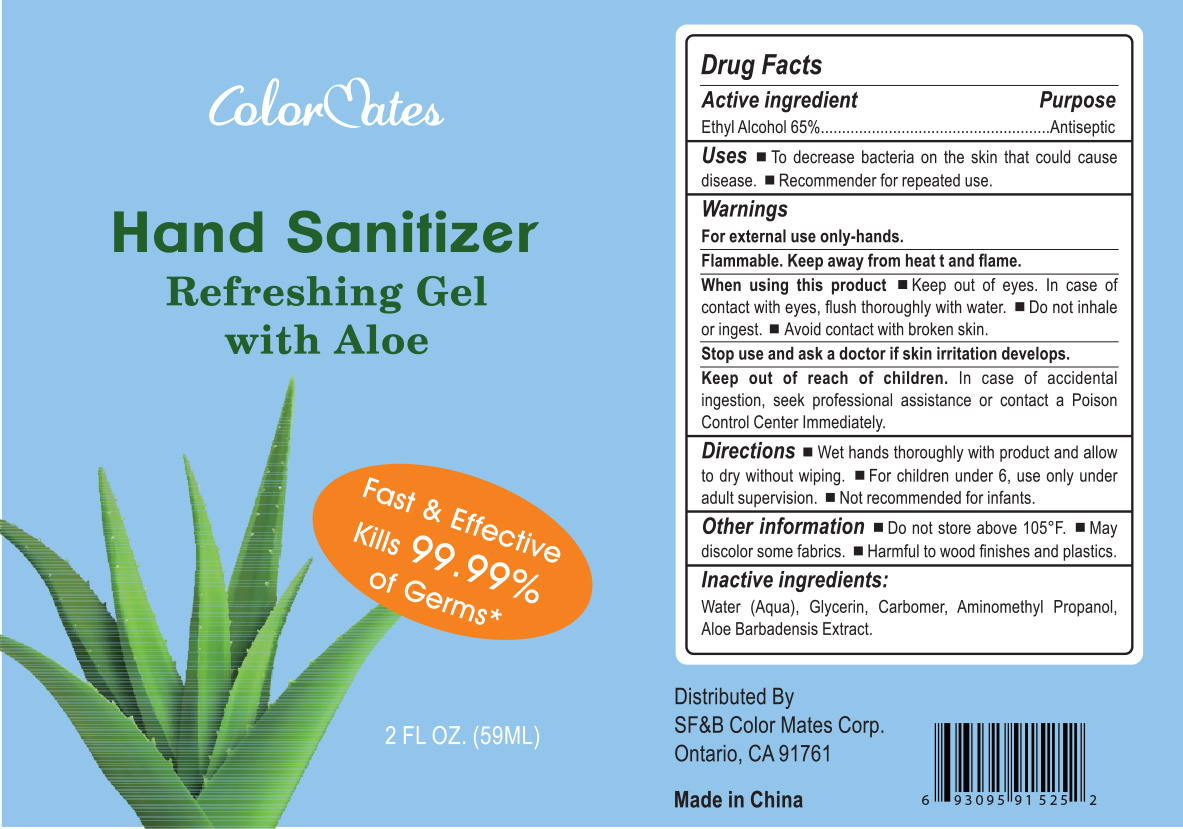 DRUG LABEL: Hand Sanitizer
NDC: 76781-001 | Form: GEL
Manufacturer: S.F. & B. COLOR MATES CORP.
Category: otc | Type: HUMAN OTC DRUG LABEL
Date: 20200424

ACTIVE INGREDIENTS: ALCOHOL 65 mL/100 mL
INACTIVE INGREDIENTS: GLYCERIN; AMINOMETHYLPROPANOL; WATER; CARBOMER HOMOPOLYMER, UNSPECIFIED TYPE; ALOE VERA LEAF

Colormates Hand Sanitizer

Active Ingredient

Ethyl Alcohol 65%

Purpose

Antiseptic

Uses

■ To decrease bacteria on the skin that could cause disease. ■ Recommended for repeated use

Warnings

For external use only-hands. Flammable. Keep away from heat or flame.

When using this product

■ Keep out of eyes. In case of contact with eyes, flush throughly with water. ■ Do not inhale or ingest. ■ Avoid contact with broken skin

Stop use and ask a doctor if

if skin irritation develops.

Keep out of reach of children

In case of accidental ingestion, seek professional assistance or contact a Poison Control Center immediately.

Directions

■ Wet hands thoroughly with product and allow to dry without wiping ■ For children under 6, use only under adult supervision ■ Not recommended for infants

Other information

■ Do not store above105ºF ■ May discolor some fabrics ■ Harmful to wood finishes and plastics

Inactive Ingredients

Water, Glycerin, Carbomer, Aminomethylpropanol, Aloe Barbadensis Extract